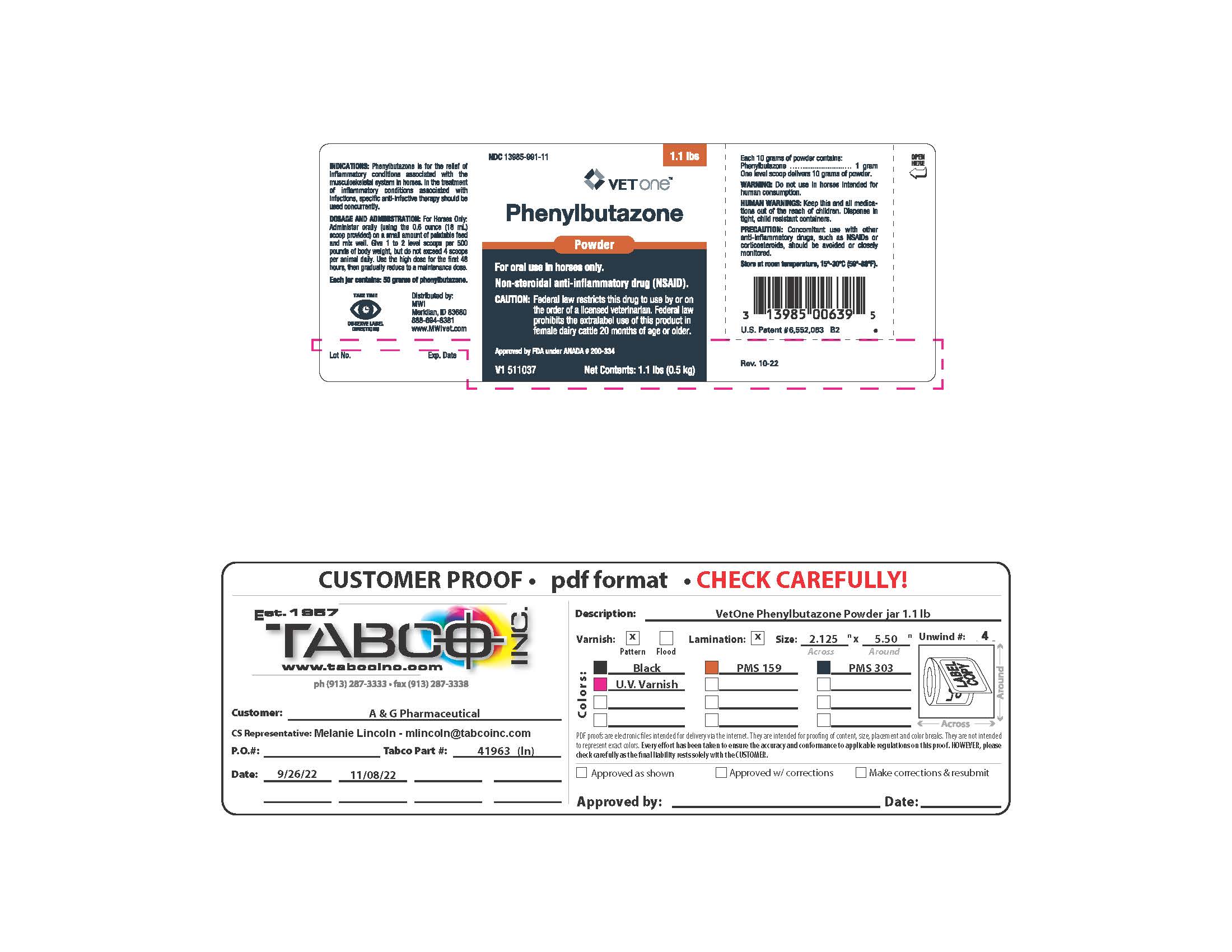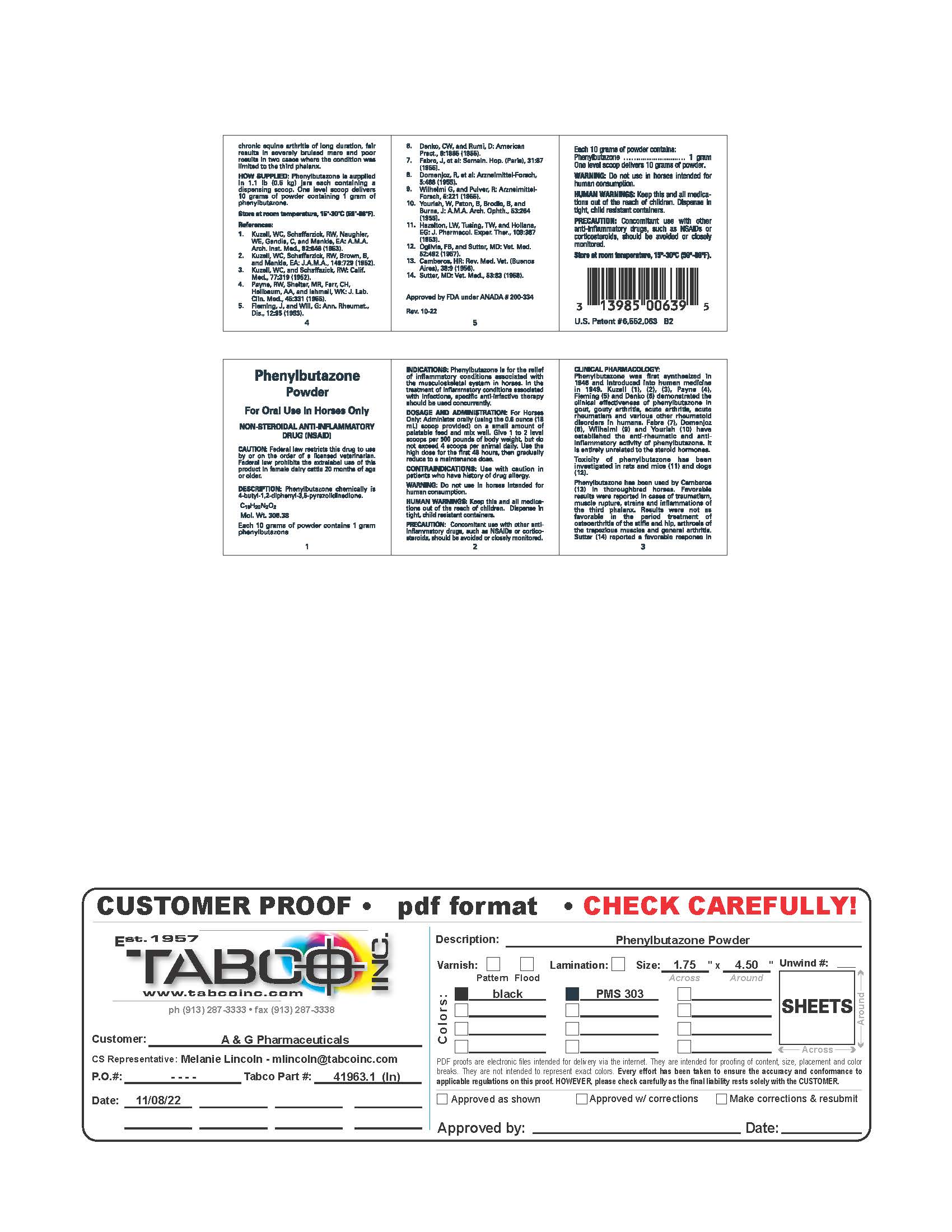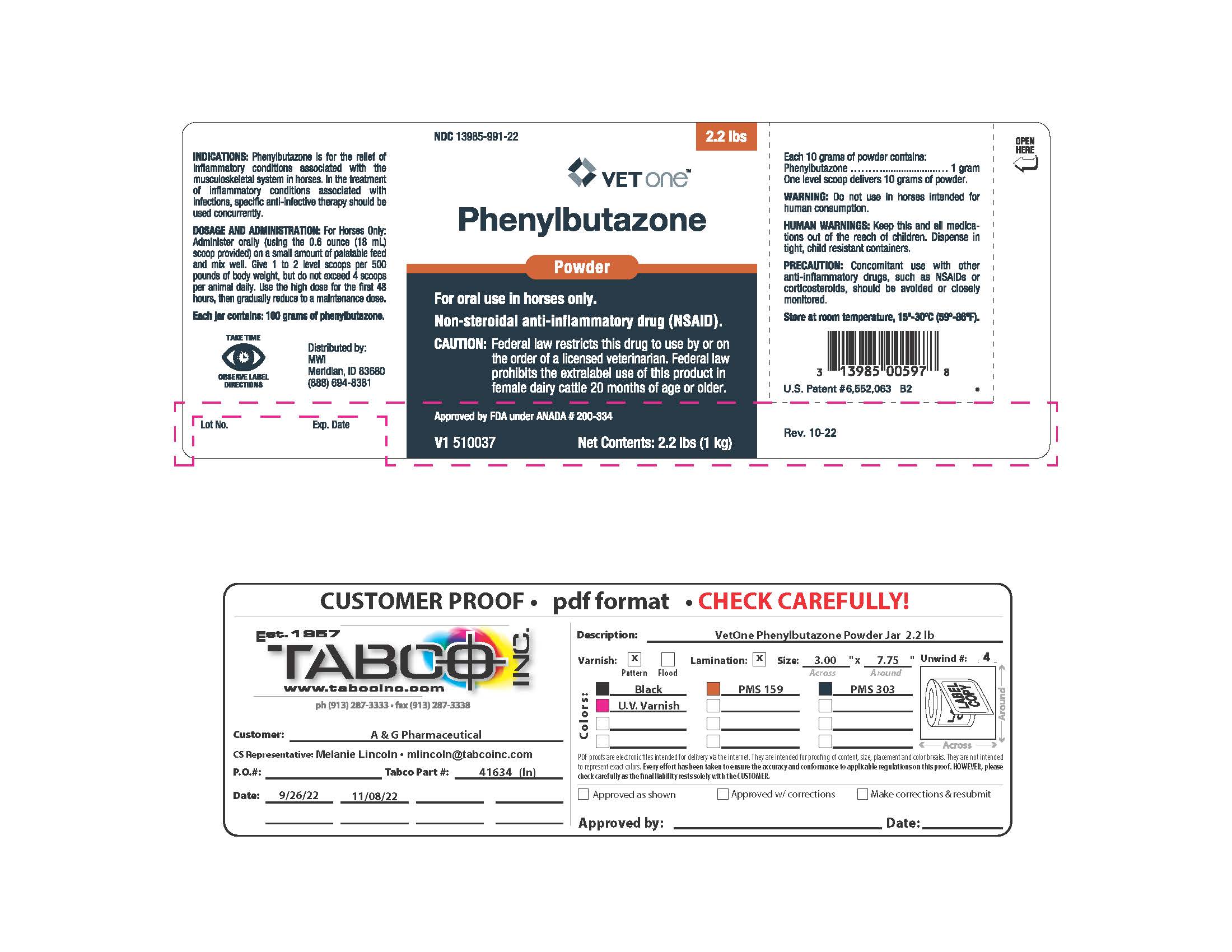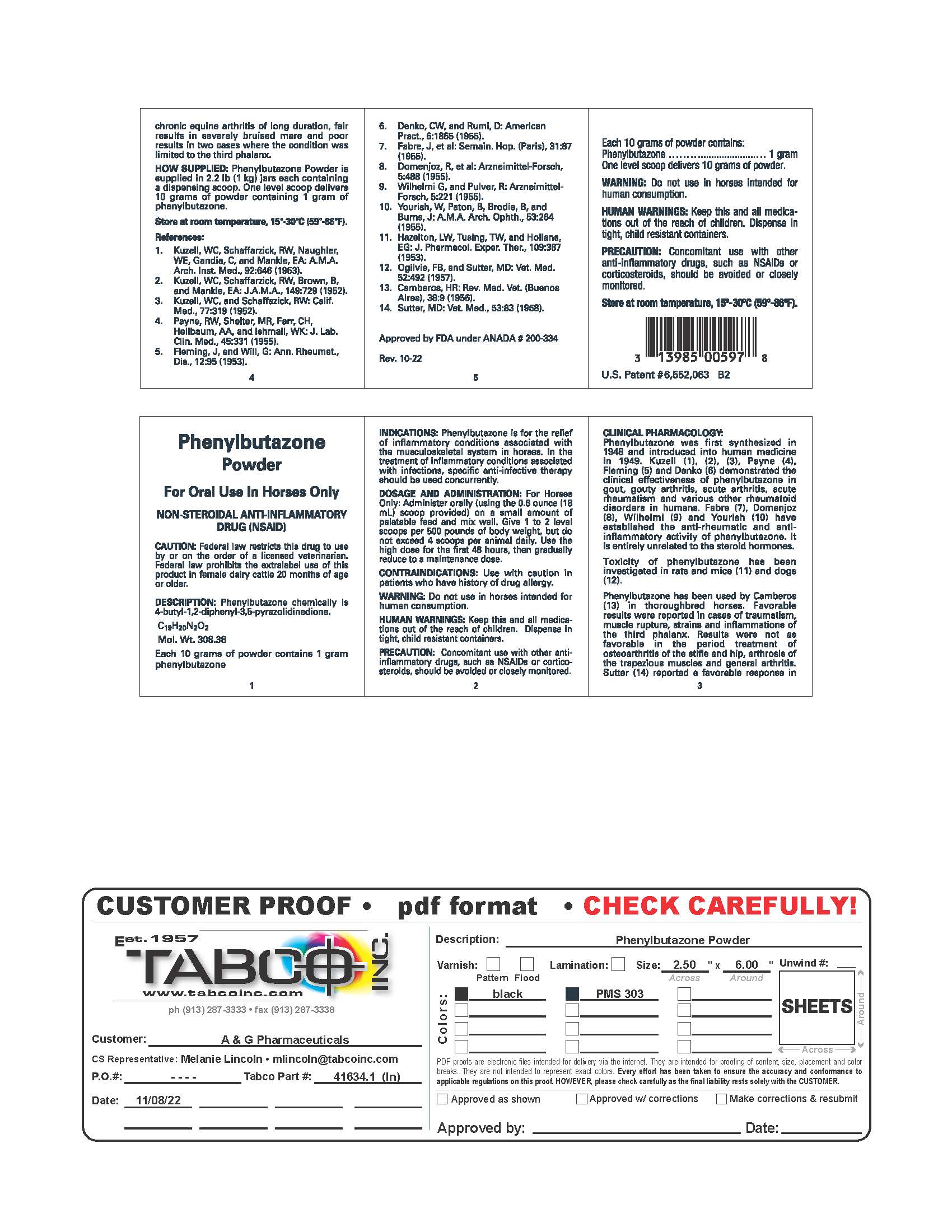 DRUG LABEL: Phenylbutazone
NDC: 13985-991 | Form: POWDER
Manufacturer: MWI/VetOne
Category: animal | Type: PRESCRIPTION ANIMAL DRUG LABEL
Date: 20250110

ACTIVE INGREDIENTS: PHENYLBUTAZONE 1 g/10 g

VETONE Phenylbutazone Powder

For Oral Use In Horses Only

NON-STEROIDAL ANTI-INFLAMMATORY DRUG (NSAID)

CAUTION: Federal law restricts this drug to use by or on the order of a licensed veterinarian. Federal law prohibits the extralabel use of this product in female dairy cattle 20 months of age or older.

DESCRIPTION

Phenylbutazone chemically is 4-butyl-1,2-diphenyl-3,5-pyrazolidinedione.
C19H20N2O2

Mol. Wt. 308.38
Each 10 grams of powder contains 1 gram phenylbutazone

INDICATIONS

Phenylbutazone is for the relief of inflammatory conditions associated with the musculoskeletal system in horses. In the treatment of inflammatory conditions associated with infections, specific anti-infective therapy should be used concurrently.

DOSAGE AND ADMINISTRATION

For Horses Only: Administer orally (using the 0.6 ounce (18 mL) scoop provided) on a small amount of palatable feed and mix well. Give 1 to 2 level scoops per 500 pounds of body weight, but do not exceed 4 scoops per animal daily. Use the high dose for the first 48 hours, then gradually reduce to a maintenance dose.

CONTRAINDICATIONS

Use with caution in patients who have a history of drug allergy.

WARNING

Do not use in horses intended for human consumption.

HUMAN WARNING

Keep this and all medications out of the reach of children. Dispense in tight, child resistant containers.

PRECAUTION

Concomitant use with other anti-inflammatory drugs, such as NSAIDs or corticosteroids, should be avoided or closely monitored.

CLINICAL PHARMACOLOGY

Phenylbutazone was first synthesized in 1948 and introduced into human medicine in 1949. Kuzell (1), (2), (3), Payne (4), Fleming (5) and Denko (6) demonstrated the clinical effectiveness of phenylbutazone in gout, gouty arthritis, acute arthritis, acute rheumatism and various other rheumatoid disorders in humans. Fabre (7), Domenjoz (8), Wilhelmi (9) and Yourish (10) have established the anti-rheumatic and anti-inflammatory activity of phenylbutazone. It is entirely unrelated to the steroid hormones.
Toxicity of phenylbutazone has been investigated in rats and mice (11) and dogs (12).
Phenylbutazone has been used by Camberos (13) in thoroughbred horses. Favorable results were reported in cases of traumatism, muscle rupture, strains and inflammations of the third phalanx. Results were not as favorable in the period treatment of osteoarthritis of the stifle and hip, arthrosis of the trapezious muscles and general arthritis. Sutter (14) reported a favorable response in chronic equine arthritis of long duration, fair results in severely bruised mare and poor results in two cases where the condition was limited to the third phalanx.

HOW SUPPLIED

Phenylbutazone Powder is supplied in 1.1 lb (0.5 kg) jars and 2.2 lb (1 kg) jars each containing a dispensing scoop. One level scoop delivers 10 grams of powder containing 1 gram of phenylbutazone.

References

1. Kuzell, WC, Schaffarzick, RW, Naughler, WE, Gandia, C, and Mankle, EA: A.M.A. Arch. Inst. Med., 92:646 (1953).
2. Kuzell, WC, Schaffarzick, RW, Brown, B, and Mankle, EA: J.A.M.A., 149:729 (1952).
3. Kuzell, WC, and Schaffarzick, RW: Calif. Med., 77:319 (1952).
4. Payne, RW, Shelter, MR, Farr, CH, Hellbaum, AA, and Ishmall, WK: J. Lab. Clin. Med., 45:331 (1955).
5. Fleming, J, and Will, G: Ann. Rheumat., Dis., 12:95 (1953).
6. Denko, CW, and Rumi, D: American Pract., 6:1865 (1955).
7. Fabre, J, et al: Semain. Hop. (Paris), 31:87 (1955).
8. Domenjoz, R, et al: Arzneimittel-Forsch, 5:488 (1955).
9. Wilhelmi, G, and Pulver, R: Arzneimittel-Forsch, 5:221 (1955).
10. Yourish, W, Paton, B, Brodie, B, and Burns, J: A.M.A. Arch. Ophth., 53:264 (1955).
11. Hazelton, LW, Tusing, TW, and Hollana, EG: J. Pharmacol. Exper. Ther., 109:387 (1953).
12. Ogilvie, FB, and Sutter, MD: Vet. Med. 52:492 (1957).
13. Camberos, HR: Rev. Med. Vet. (Buenos Aries), 38:9 (1956).
14. Sutter, MD: Vet. Med., 53:83 (1958).

Approved by FDA under ANADA # 200-334

Principal Display Panel - Phenylbutazone Powder (1.1 lb jar)

NDC 13985-991-11

VETONE

Phenylbutazone

Powder

For Oral Use In Horses Only

NON-STEROIDAL ANTI-INFLAMMATORY DRUG (NSAID)

CAUTION: Federal law restricts this drug to use by or on the order of a licensed veterinarian. Federal law prohibits the extralabel use of this product in female dairy cattle 20 months of age or older.

Approved by FDA under ANADA # 200-334

Net Contents: 1.1 lb (0.5 kg)

Principal Display Panel - Phenylbutazone Powder (2.2 lb jar)

NDC 13985-991-22

VETONE™

Phenylbutazone

Powder

For Oral Use In Horses Only

NON-STEROIDAL ANTI-INFLAMMATORY DRUG (NSAID).

CAUTION: Federal law restricts this drug to use by or on the order of a licensed veterinarian. Federal law prohibits the extralabel use of this product in female dairy cattle 20 months of age or older.

Approved by FDA under ANADA # 200-334

Net Contents: 2.2 lb (1 kg)